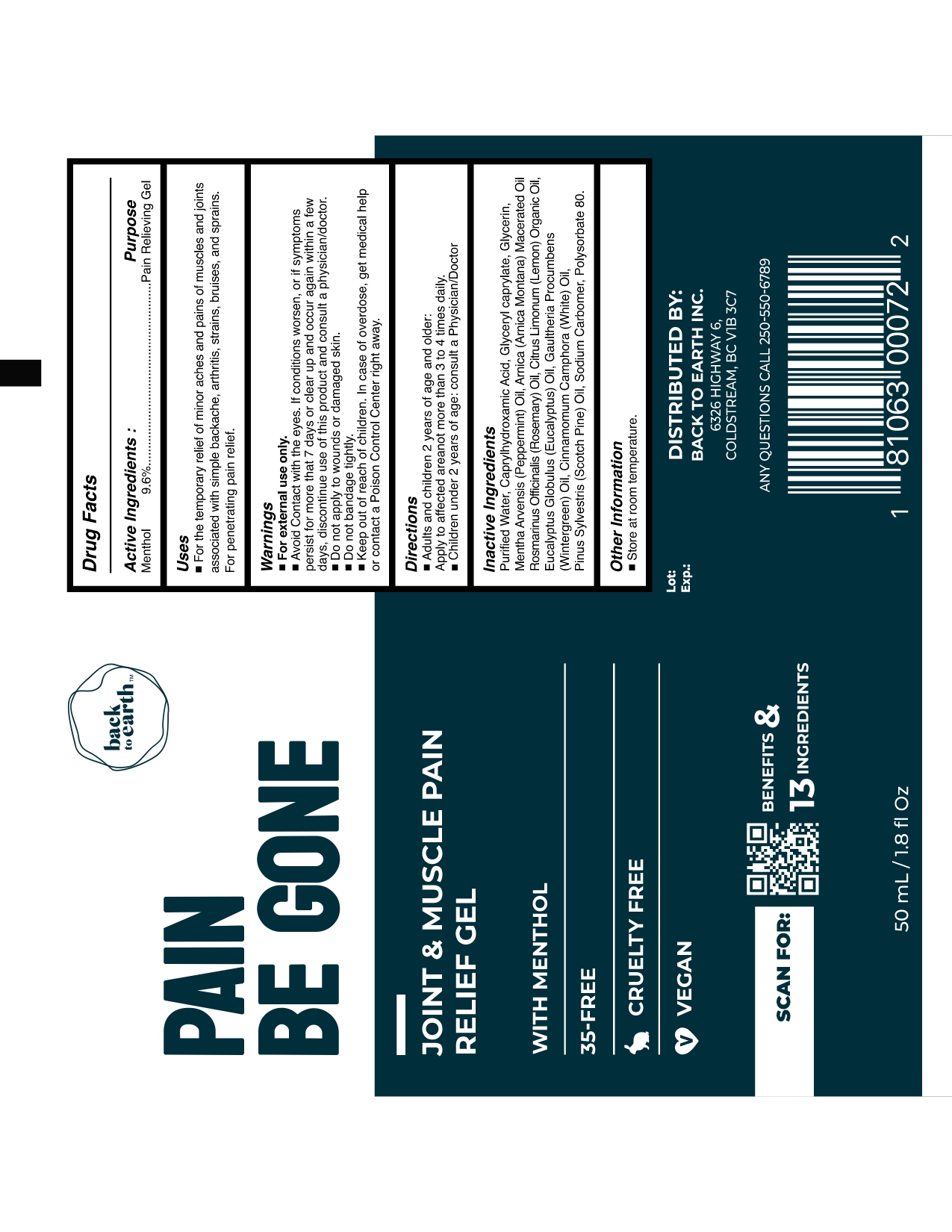 DRUG LABEL: Pain Be Gone
NDC: 82721-001 | Form: CREAM
Manufacturer: Back to Earth Inc.
Category: otc | Type: HUMAN OTC DRUG LABEL
Date: 20250129

ACTIVE INGREDIENTS: MENTHOL 9.6 mg/1 mL
INACTIVE INGREDIENTS: CAPRYLHYDROXAMIC ACID; GLYCERIN; CITRUS LIMON FRUIT OIL; ROSMARINUS OFFICINALIS FLOWERING TOP OIL; EUCALYPTUS OIL; GAULTHERIA PROCUMBENS LEAF; WATER; CARBOMER HOMOPOLYMER, UNSPECIFIED TYPE; METHYL SALICYLATE; ARNICA MONTANA; CAMPHOR OIL, WHITE; PINE NEEDLE OIL (PINUS SYLVESTRIS); POLYSORBATE 80; CAPRYLYL GLYCOL; GLYCERYL CAPRYLATE; MENTHA PIPERITA

back to earth

Active Ingredients

Menthol 9.6%

PURPOSE

Pain Relieving Gel

WARNINGS

■ For external use only.
■ Avoid Contact with the eyes. If conditions worsen, or if symptoms
persist for more that 7 days or clear up and occur again within a few
days, discontinue use of this product and consult a physician/doctor.
■ Do not apply to wounds or damaged skin.

■ Do not bandage tightly.

■ Keep out of reach of children. In case of overdose, get medical help
or contact a Poison Control Center right away.

DOSAGE AND ADMINISTRATION

■ Adults and children 2 years of age and older:
Apply to affected area not more than 3 to 4 times daily.
■ Children under 2 years of age: consult a Physician/Doctor

INDICATIONS AND USAGE

■ For the temporary relief of minor aches and pains of muscles and joints
associated with simple backache, arthritis, strains, bruises, and sprains.
For penetrating pain relief.

INACTIVE INGREDIENT

Purified Water, Caprylhydroxamic Acid, Glyceryl caprylate, Glycerin,
Mentha Arvensis (Peppermint) Oil, Arnica (Arnica Montana) Macerated Oil
Rosmarinus Officinalis (Rosemary) Oil, Citrus Limonum (Lemon) Organic Oil,
Eucalyptus Globulus (Eucalyptus) Oil, Gaultheria Procumbens
(Wintergreen) Oil, Cinnamomum Camphora (White) Oil,
Pinus Sylvestris (Scotch Pine) Oil, Sodium Carbomer, Polysorbate 80.

■ Keep out of reach of children. In case of overdose, get medical help
or contact a Poison Control Center right away.